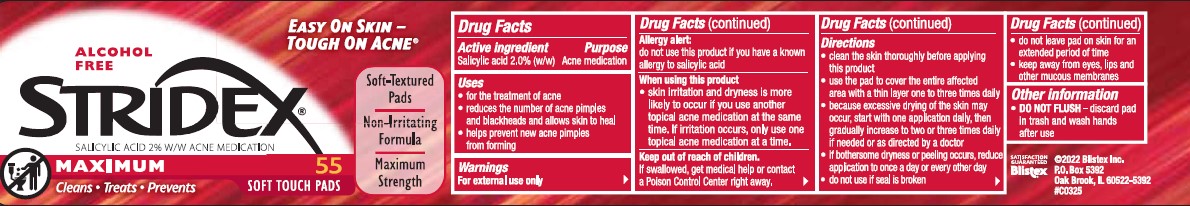 DRUG LABEL: Stridex Essential
NDC: 44038-2119 | Form: LIQUID
Manufacturer: Accupac LLC
Category: otc | Type: HUMAN OTC DRUG LABEL
Date: 20240918

ACTIVE INGREDIENTS: SALICYLIC ACID 1 g/100 mL
INACTIVE INGREDIENTS: ETHYLHEXYLGLYCERIN; EDETATE SODIUM; SODIUM CITRATE; WATER; AMMONIUM XYLENESULFONATE; AMMONIUM LAURYL SULFATE; PHENOXYETHANOL; SODIUM HYDROXIDE; MENTHOL; SILICON DIOXIDE; SODIUM ASCORBYL PHOSPHATE; .ALPHA.-TOCOPHEROL ACETATE

Active ingredient

Salicylic Acid 1.0%(w/w)

Purpose

Acne medication

Uses

for the treatment of acne

reduces the number of acne pimples and blackheads and allows skin to heal

helps prevent new acne pimples from forming

Warnings

Allergy alert:

do not use this product if you have a known allergy to salicylic acid

When using this product

skin irritation and dryness is more likely to occur if you use another topical acne medication at the same time. If irritation occurs, only use one topical acne medication at a time.

Keep out of the reach of children.

If swallowed, get medical help or contact a Poison Control Center right away.

Directions

-clean the skin thoroughly before applying this product

-use the pad to cover the entire affected area with a thin layer one to three times daily

-because excessive drying of the skin may occur, start with one application daily, then gradually increase to two or three times daily if needed of as directed by a doctor

-if bothersome dryness or peeling occurs, reduce application to once a day or every other day

-do not use if seal is broken

-do not leave pad on skin for an extended period of tme

-keep away from eyes, lips and other mucous membranes

Other information

DO NOT FLUSH-discard pad in trash and wash hands after use

Inactive ingredients

Water

Ammonium Xylenesulfonate

Ammonium Lauryl Sulfate

Sodium Citrate

Phenoxyethanol

Ethylhexyglycerin

Sodium Hydroxide

Menthol

Silicon dioxide

Sodium Ascorbyl Phosphate

Edetate Sodium

Alpha-Tocopherol acetate